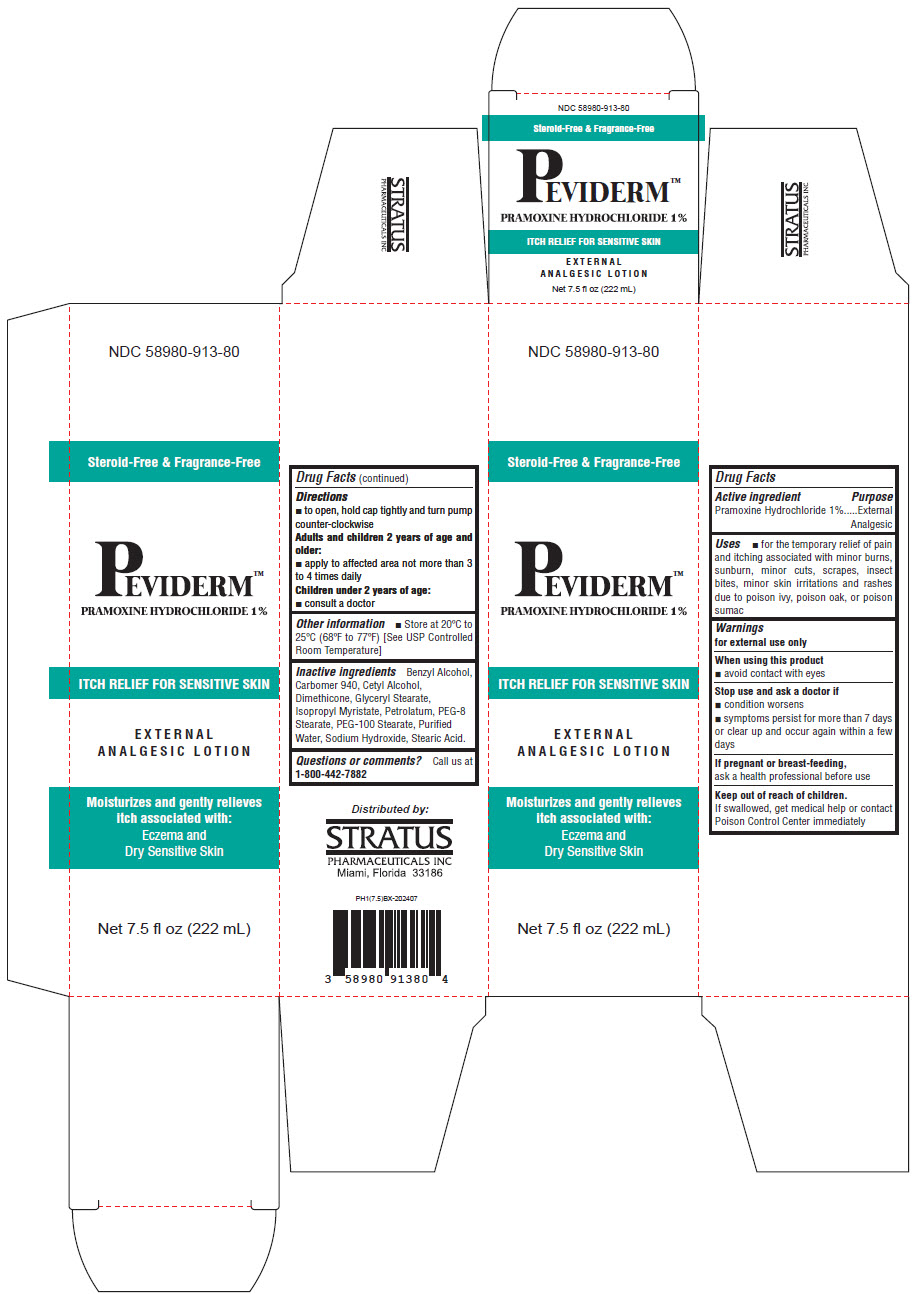 DRUG LABEL: Peviderm Pramoxine Hydrocholride 1%
NDC: 58980-913 | Form: LOTION
Manufacturer: Stratus Pharmaceuticals Inc
Category: otc | Type: HUMAN OTC DRUG LABEL
Date: 20241107

ACTIVE INGREDIENTS: Pramoxine Hydrochloride 1 mg/1 mL
INACTIVE INGREDIENTS: Water; Glyceryl Stearate/PEG-100 Stearate; PEG-8 Stearate; Calcium Chloride; CARBOMER HOMOPOLYMER TYPE C (ALLYL PENTAERYTHRITOL CROSSLINKED); Cetyl Palmitate; Isopropyl Myristate; White Petrolatum; Stearic Acid; Benzyl Alcohol; Sodium Hydroxide

Peviderm Pramoxine Hydrocholride 1%

Drug Facts

Active ingredient

Pramoxine Hydrochloride 1%

Purpose

External Analgesic

Uses

- for the temporary relief of pain and itching associated with minor burns, sunburn, minor cuts, scrapes, insect bites, minor skin irritations and rashes due to poison ivy, poison oak, or poison sumac

Warnings

for external use only

When using this product

- avoid contact with eyes

Stop use and ask a doctor if

- condition worsens
- symptoms persist for more than 7 days or clear up and occur again within a few days

PREGNANCY OR BREAST FEEDING

If pregnant or breast-feeding, ask a health professional before use

Keep out of reach of children.

If swallowed, get medical help or contact Poison Control Center immediately

Directions

- to open, hold cap tightly and turn pump counter-clockwise

Adults and children 2 years of age and older:

- apply to affected area not more than 3 to 4 times daily

Children under 2 years of age:

- consult a doctor

Other information

- Store at 20°C to 25°C (68°F to 77°F) [See USP Controlled Room Temperature]

Inactive ingredients

Benzyl Alcohol, Carbomer 940, Cetyl Alcohol, Dimethicone, Glyceryl Stearate, Isopropyl Myristate, Petrolatum, PEG-8 Stearate, PEG-100 Stearate, Purified Water, Sodium Hydroxide, Stearic Acid.

Questions or comments?

Call us at 1-800-442-7882

Distributed by:
STRATUS
PHARMACEUTICALS INC
Miami, Florida 33186

PRINCIPAL DISPLAY PANEL - 222 mL Bottle Box

NDC 58980-913-80

Steroid-Free & Fragrance-Free

PEVIDERM™
PRAMOXINE HYDROCHLORIDE 1%

ITCH RELIEF FOR SENSITIVE SKIN

EXTERNAL
ANALGESIC LOTION

Moisturizes and gently relieves
itch associated with:
Eczema and
Dry Sensitive Skin

Net 7.5 fl oz (222 mL)